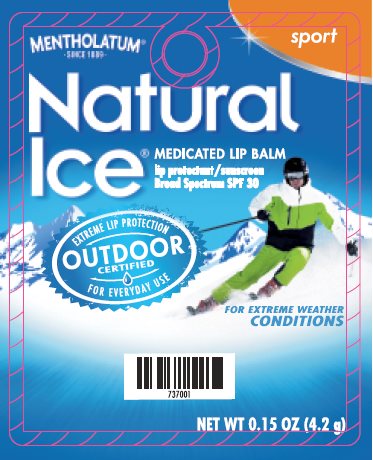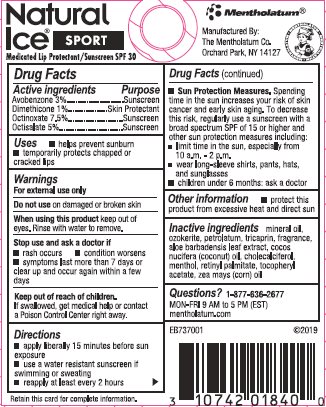 DRUG LABEL: Mentholatum Natural Ice
NDC: 10742-8980 | Form: OINTMENT
Manufacturer: The Mentholatum Company
Category: otc | Type: HUMAN OTC DRUG LABEL
Date: 20241217

ACTIVE INGREDIENTS: AVOBENZONE 30 mg/1 g; DIMETHICONE 10 mg/1 g; OCTINOXATE 75 mg/1 g; OCTISALATE 50 mg/1 g
INACTIVE INGREDIENTS: MINERAL OIL; CERESIN; PETROLATUM; TRICAPRIN; ALOE VERA LEAF; COCONUT OIL; CALCIFEDIOL; LEVOMENTHOL; VITAMIN A PALMITATE; .ALPHA.-TOCOPHEROL; CORN OIL

Drug Facts - Mentholatum Natural Ice Sport SPF 30

Active ingredients

Avobenzone 3%

Dimethicone 1%

Octinoxate 7.5%

Octisalate 5%

Purpose

Avobenzone - Sunscreen

Dimethicone - Skin protectant

Octinoxate - Sunscreen

Octisalate - Sunscreen

Uses

- helps prevent sunburn
- temporarily protects chapped or cracked lips

Warnings

For external use only

Do not use

on damaged or broken skin

When using this product

keep out of eyes. Rinse with water to remove.

Stop use and ask a doctor if

- rash occurs
- condition worsens
- symptoms last more than 7 days or clear up and occur again within a few days

Keep out of reach of children.

If swallowed, get medical help or contact a Poison Control Center right away.

Directions

- apply liberally 15 minutes before sun exposure
- use a water resistant sunscreen if swimming or sweating
- reapply at least every 2 hours
- Sun Protection Measures. Spending time in the sun increases your risk of skin cancer and early skin aging. To decrease this risk, regularly use a sunscreen with a broad spectrum SPF of 15 or higher and other sun protection measures including:
- limit time in the sun, especially from 10 a.m. – 2 p.m.
- wear long-sleeve shirts, pants, hats, and sunglasses
- children under 6 months: ask a doctor

Other information

- protect this product from excessive heat and direct sun

Inactive ingredients

mineral oil, ozokerite, petrolatum, tricaprin, fragrance, aloe barbadensis leaf extract, cocos nucifera (coconut) oil, cholecalciferol, menthol, retinyl palmitate, tocopheryl acetate, zea mays (corn) oil

Questions?

1-877-636-2677

MON-FRI 9 AM to 5 PM (EST)

mentholatum.com